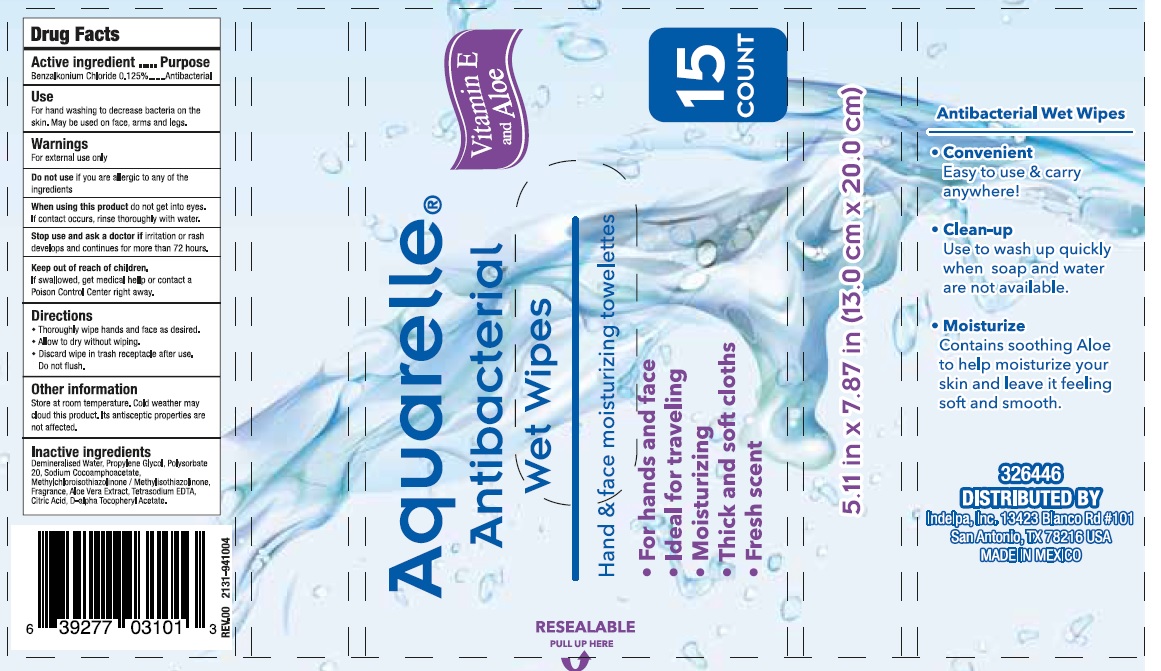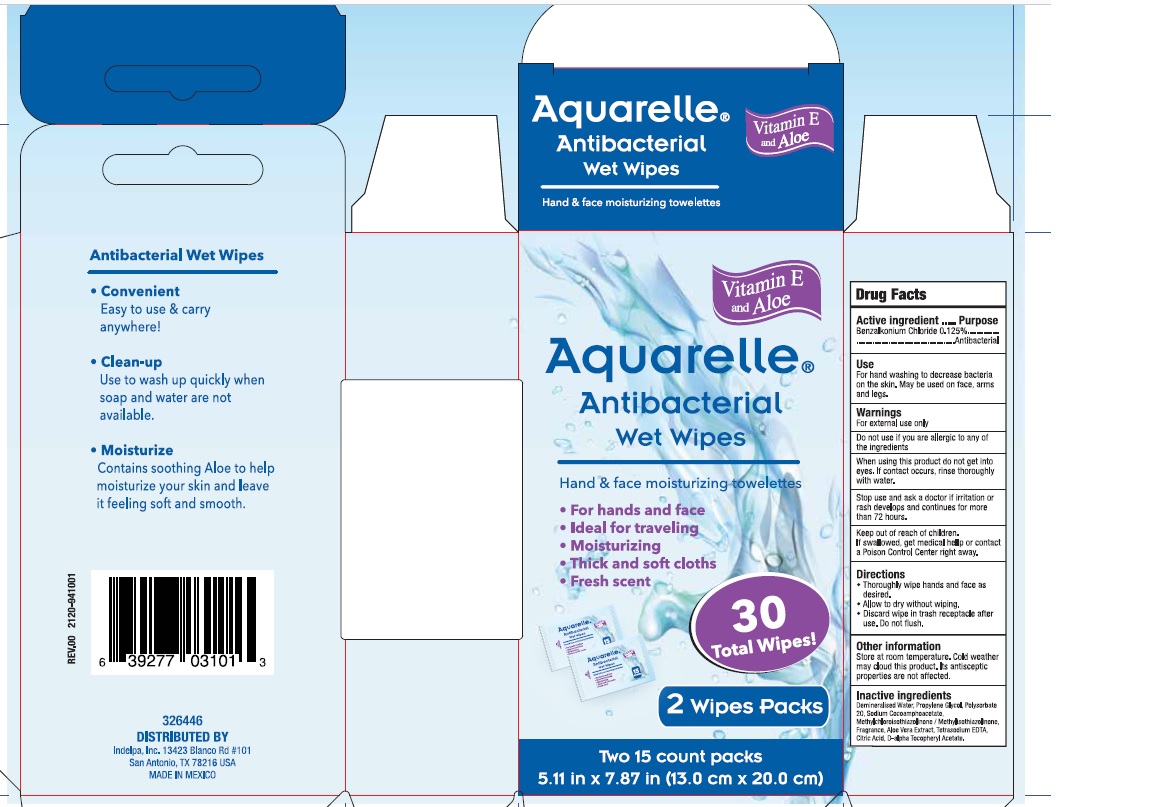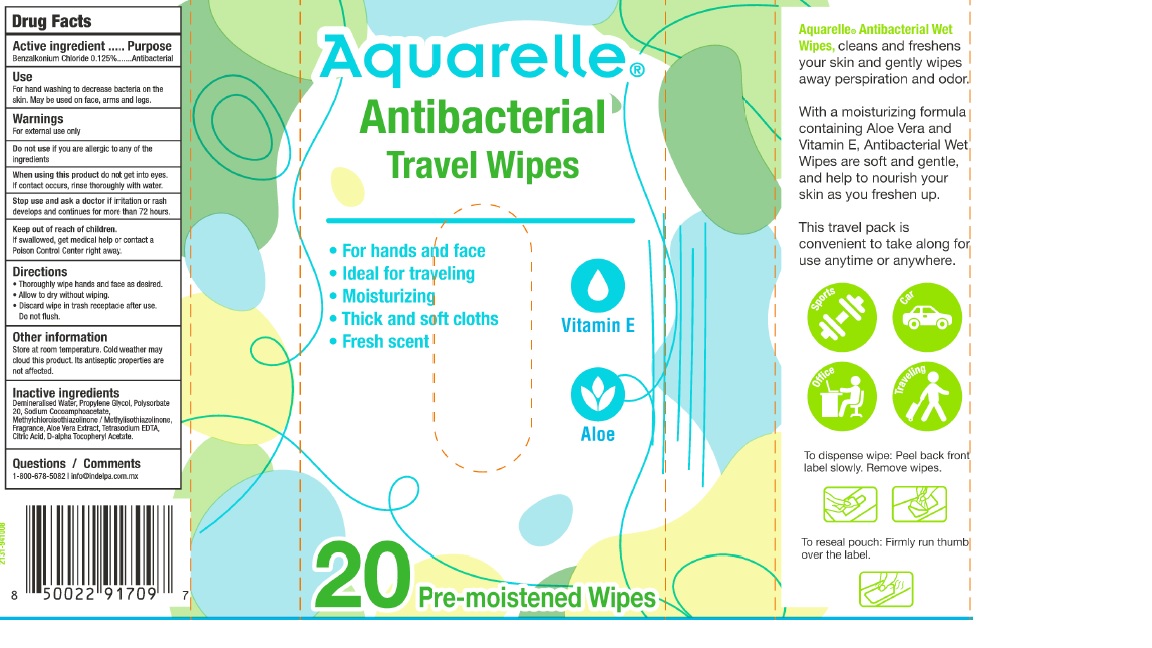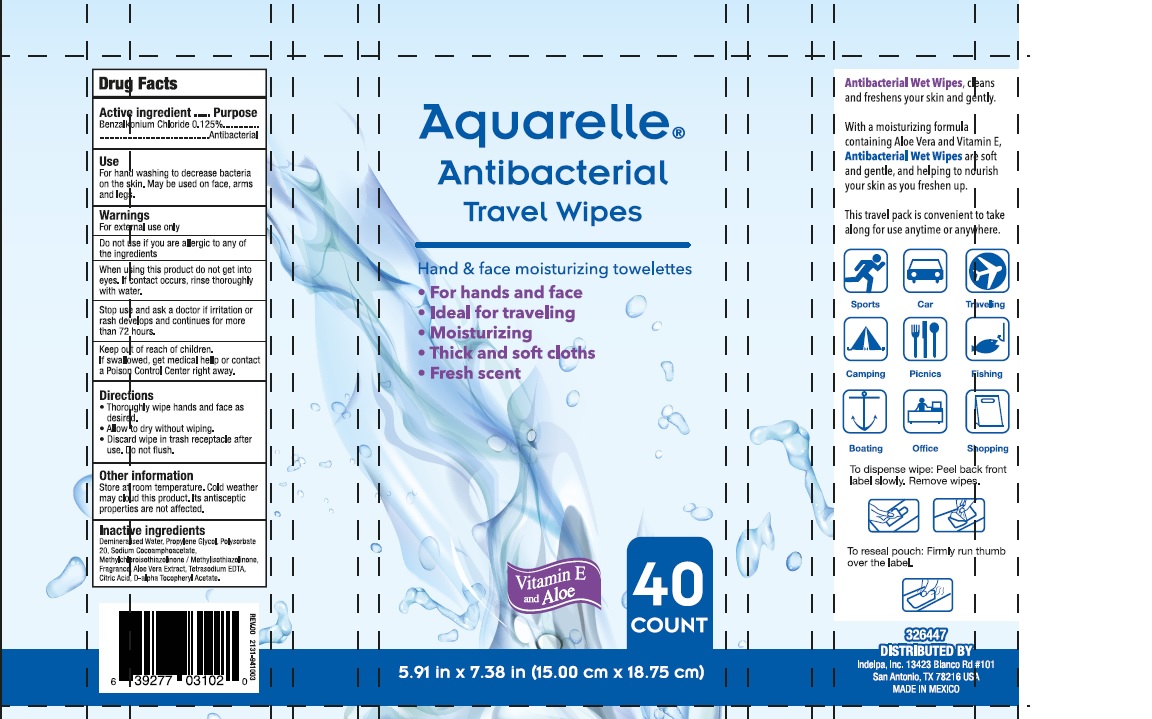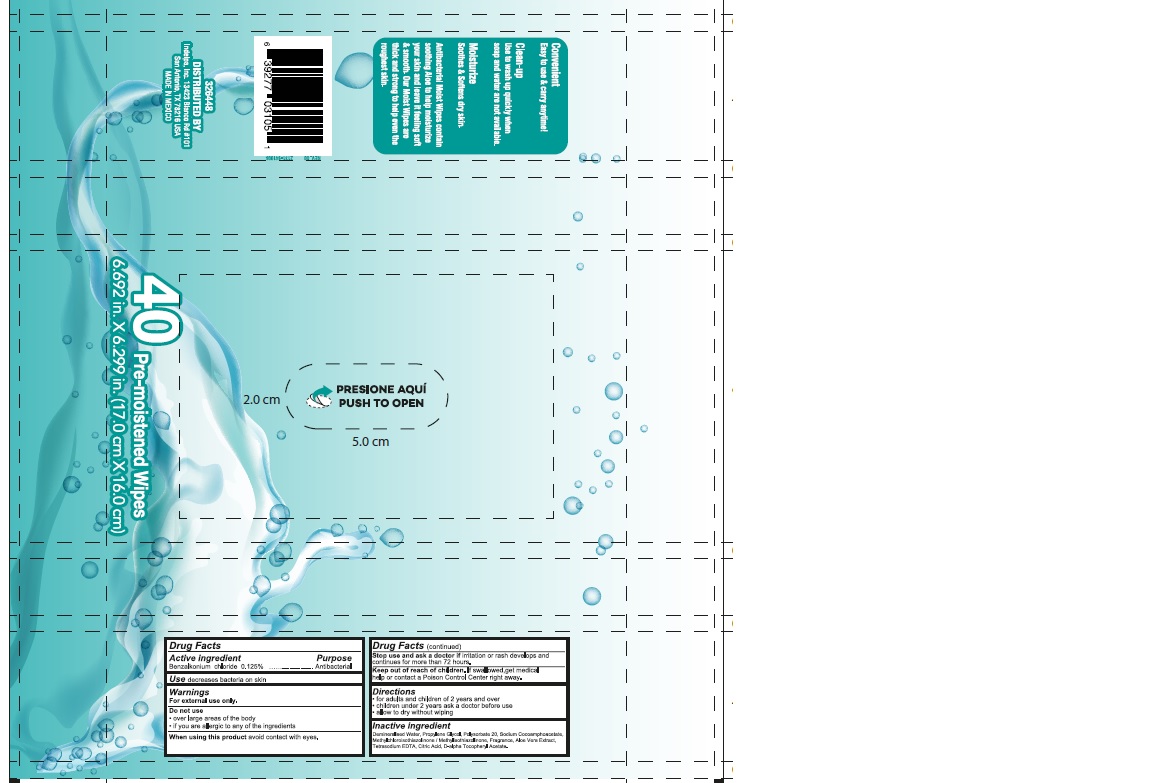 DRUG LABEL: AQUARELLE
NDC: 70697-805 | Form: CLOTH
Manufacturer: INDELPA, S.A DE C.V
Category: otc | Type: HUMAN OTC DRUG LABEL
Date: 20230110

ACTIVE INGREDIENTS: BENZALKONIUM CHLORIDE 0.125 mg/100 mg
INACTIVE INGREDIENTS: WATER 98.567 mg/100 mg; ALOE VERA LEAF 0.05 mg/100 mg; POLYSORBATE 20 0.3 mg/100 mg; .ALPHA.-TOCOPHEROL ACETATE, DL- 0.01 mg/100 mg; CITRIC ACID MONOHYDRATE 0.018 mg/100 mg; METHYLCHLOROISOTHIAZOLINONE/METHYLISOTHIAZOLINONE MIXTURE 0.1 mg/100 mg; SODIUM COCOAMPHOACETATE 0.2 mg/100 mg; EDETATE SODIUM 0.03 mg/100 mg; PROPYLENE GLYCOL 0.5 mg/100 mg

ACTIVE INGREDIENT

Benzalkonium Chloride....0.125%

PURPOSE

Antibaterial

INDICATIONS AND USAGE

For hand washing to decrease bacteria on the skin. May be used on face, arms and legs

WARNINGS AND PRECAUTIONS

for external use only

DO NOT USE

If you are allergic to any of the ingredients

WHEN USING

Di not get into eyes. If contact occurs rinse thoroughly with water

STOP USE

If irritation or rash develops and continues for more than 72 hours

ASK DOCTOR

If irritation or rash develops and continues for more than 72 hours

KEEP OUT OF REACH OF CHILDREN

If swallowed, get medical help or Contact a Poison Control Center right away

INDICATIONS AND USAGE

Throughly wipe hands and face as desired.

Allow to dry without wiping.

Discard wipe in trash receptacle after use. Do not flush

STORAGE AND HANDLING

Store at room temperature. Cold weather may cloud this product. It´s antisceptic properties are not affected

INACTIVE INGREDIENT

Demineralised water, Propylene Glycol, Polysorbate 20, Sodium Cocoamphoacetate, Methylchloroisothiazolinone / Methylisothiazolinone, Fragrance, Aloe Vera Extract, Tretasodium EDTA, Citric Acid, D-alpha Tocopheryl Acetate.

DOSAGE AND ADMINISTRATION

Dossage: swab

Administration: Topical

INSTRUCTIONS FOR USE

To dispense wipe: Peel back front label slowly. Remove wipes

To resela Pouch: Firmly run thumb over the label

WARNINGS

For external use only